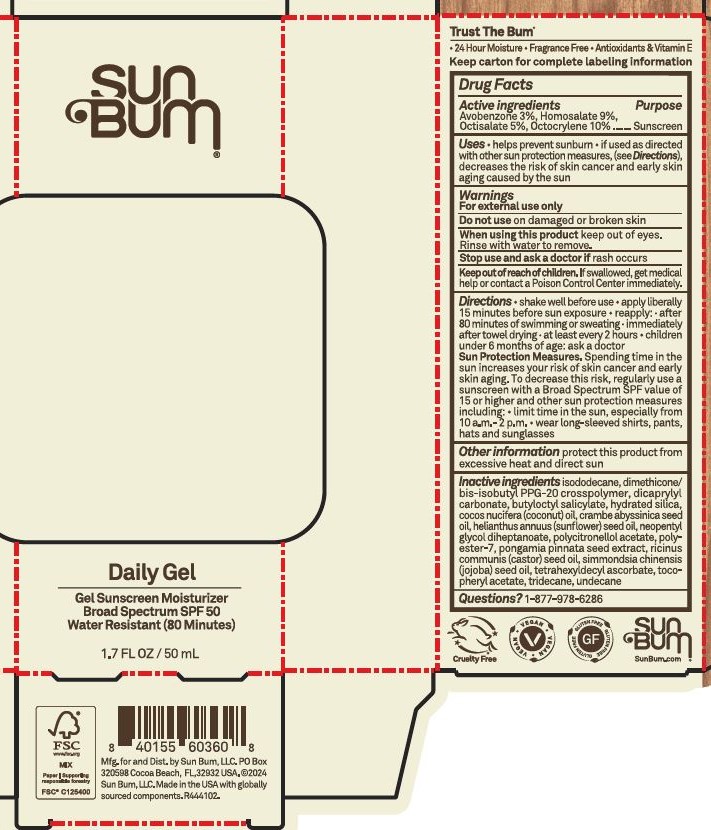 DRUG LABEL: Sun Bum Daily Gel Gel Sunscreen Moisturizer Broad Spectrum SPF 50
NDC: 69039-662 | Form: GEL
Manufacturer: Sun Bum, LLC
Category: otc | Type: HUMAN OTC DRUG LABEL
Date: 20250923

ACTIVE INGREDIENTS: OCTISALATE 50 mg/1 mL; OCTOCRYLENE 100 mg/1 mL; AVOBENZONE 30 mg/1 mL; HOMOSALATE 90 mg/1 mL
INACTIVE INGREDIENTS: NEOPENTYL GLYCOL DIHEPTANOATE; PONGAMIA PINNATA SEED; ISODODECANE; DICAPRYLYL CARBONATE; TRIDECANE; TETRAHEXYLDECYL ASCORBATE; CRAMBE HISPANICA SUBSP. ABYSSINICA SEED OIL; SUNFLOWER OIL; UNDECANE; CASTOR OIL; COCONUT OIL; JOJOBA OIL; BUTYLOCTYL SALICYLATE; CITRONELLOL ACETATE, (S)-; ALPHA-TOCOPHEROL ACETATE; HYDRATED SILICA; DIMETHICONE/BIS-ISOBUTYL PPG-20 CROSSPOLYMER; POLYESTER-7

Sun Bum Daily Gel Gel Sunscreen Moisturizer Broad Spectrum SPF 50

Active Ingredients

Avobenzone 3%, Homosalate 9%,

Octisalate 5%, Octocrylene 10%

Purpose

Sunscreen

Uses

• helps prevent sunburn

• if used as directed with other sun protection measures, (see Directions), decreases the risk of skin cancer and early skin aging caused by the sun

Warnings

For external use only

Do not use on damaged or broken skin

When using this product keep out of eyes. Rinse with water to remove.

Stop use and ask a doctor if rash occurs

Keep out of reach of children. If swallowed, get medical help or contact a Poison Control Center immediately.

Warning

Keep Out Of Reach Of Children

Directions

• shake well before use

• apply liberally 15 minutes before sun exposure

• reapply: • after 80 minutes of swimming or sweating • immediately after towel drying • at least every 2 hours

• children under 6 months of age: ask a doctor
• Sun Protection Measures. Spending time in the sun increases your risk of skin cancer and early skin aging. To decrease this risk, regularly use a sunscreen with a Broad Spectrum SPF value of 15 or higher and other sun protection measures including:

• limit time in the sun, especially from 10 a.m.- 2 p.m.

• wear long-sleeved shirts, pants,
hats and sunglasses

Directions

• shake well before use

• apply liberally 15 minutes before sun exposure

Other information

protect this product from excessive heat and direct sun

Inactive ingredients

isododecane, dimethicone/bis-isobutyl PPG-20 crosspolymer, dicaprylyl carbonate, butyloctyl salicylate, hydrated silica, cocos nucifera (coconut) oil, crambe abyssinica seed oil, helianthus annuus (sunflower) seed oil, neopentyl glycol diheptanoate, polycitronellol acetate, polyester-7, pongamia pinnata seed extract, ricinus communis (castor) seed oil, simmondsia chinensis (jojoba) seed oil, tetrahexyldecyl ascorbate, tocopheryl acetate, tridecane, undecane

Questions?

1-877-978-6286